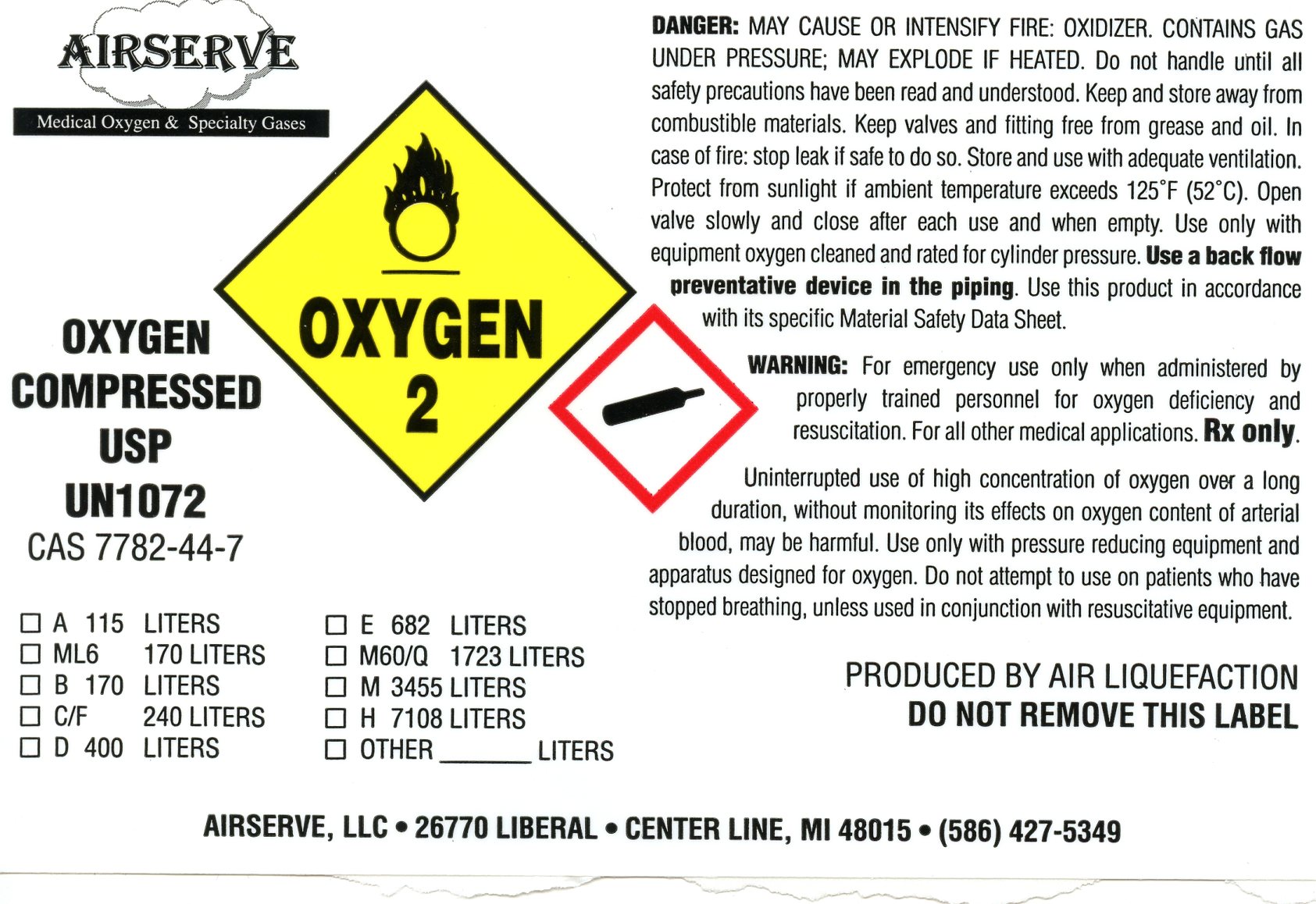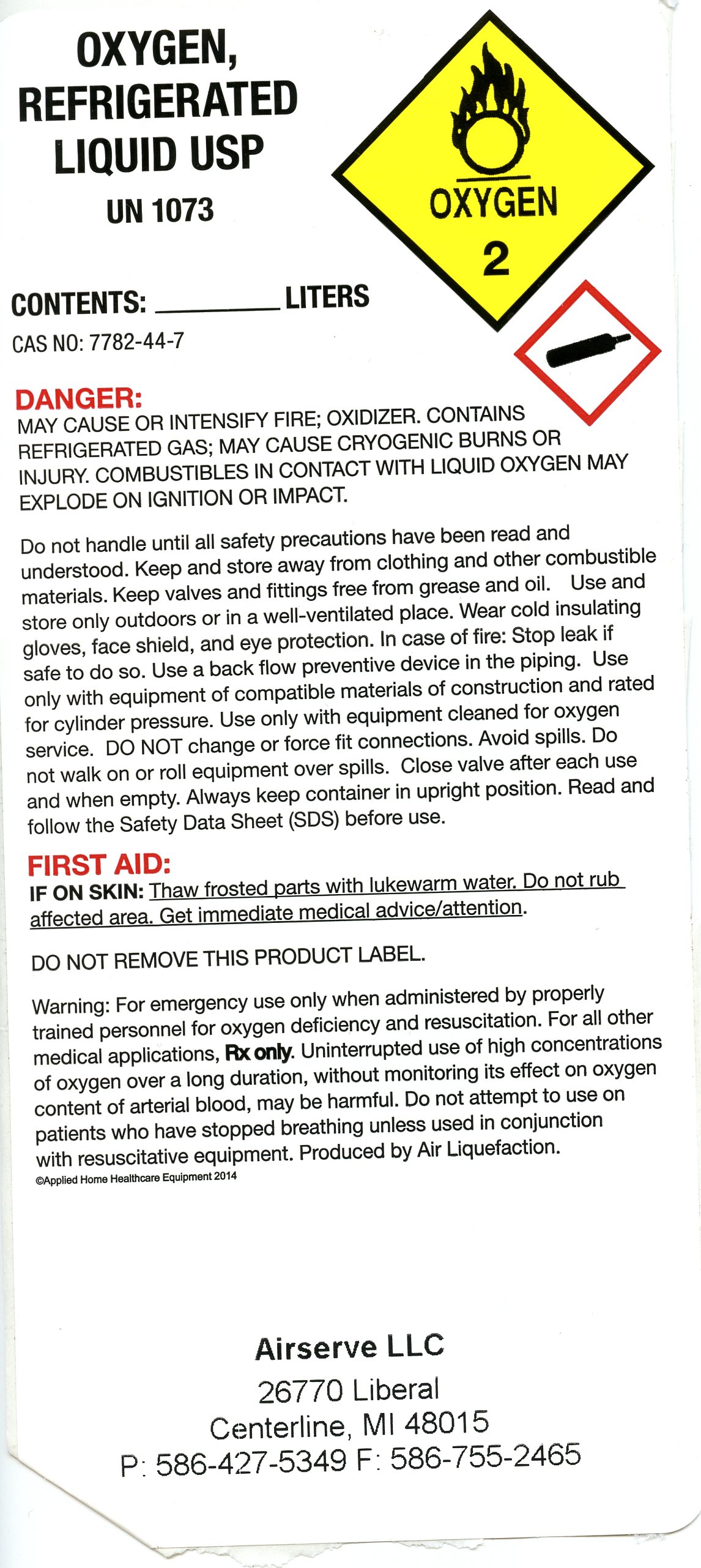 DRUG LABEL: OXYGEN
NDC: 67711-001 | Form: GAS
Manufacturer: AIRSERVE, LLC
Category: prescription | Type: HUMAN PRESCRIPTION DRUG LABEL
Date: 20191218

ACTIVE INGREDIENTS: OXYGEN 991 mL/1 L

Gaseous Oxygen Fill Label

Gaseous Oxygen Fill Label

Warning: For emergency use only when administered by properly trained personnel for oxygen deficiency and resuscitation. For all other medical applications Rx only.

Uninterrupted use of high concentration of oxygen over a long duration, without monitoring its effects on oxygen content of arterial blood, may be harmful. Use only with pressure reducing equipment and apparatus designed for oxygen. Do not attempt to use on patients who have stopped breathing, unless use in conjunction with resuscitative equipment.

WARNING: HIGH PRESSURE OXIDIZING GAS. VIGOROUSLY ACCELERATES COMBUSTION.

Keep away from oil, grease and all potential sources of ignition. Open valve slowly and close after each use and when empty. Store and use with adequate ventilation. Cylinder temperature should not exceed 125F (52C). Use only with equipment cleaned rated for cylinder pressure. Use a back flow preventative device in the piping. Use this product in accordance with its specific Material Safety Data Sheet

CAS 7782-44-7

PRODUCED BY AIR LIQUIFICATION

DO NOT REMOVE THIS LABEL

AIRSERVE, LLC 26770 LIBERAL CENTER LINE, MI 48015 (586) 427-5349

A 115 LITERS ML6 170 LITERS B 170 LITERS C/F 240 LITERS D 400 LITERS E 682 LITERS M60/Q 1723 LITERS M 3455 LITERS H 7108 LITERS OTHER ___________ LITERS

Liquid Oxygen Fill Label

OXYGEN, REFRIGERATED LIQUID

USP

UN1073

ALWAYS KEEP CONTAINER IN UPRIGHT POSITION

WARNING: For emergency use only when administered by properly trained personnel for oxygen deficiency and resuscitation. For all other medical applications, RX only.

CAUTION: Federal Law prohibits dispensing without prescription. Uninterrupted use of high concentrations of oxygen over a long duration, without monitoring its effect on oxygen content of arterial blood, may be harmful. Use only with pressure reducing equipment and apparatus designed for oxygen. Do not attempt to use on patients who have stopped breathing, unless in conjunction with resuscitative equipment. Produced by Air Liquefaction.

WARNING: EXTREMELY COLD OXIDIZING LIQUID AND GAS UNDER PRESSURE. VIGOROUSLY ACCELERATES COMBUSTION. COMBUSTIBLES IN CONTACT WITH LIQUID OXYGEN MAY EXPLODE ON IGNITION OR IMPACT. CAN CAUSE SEVERE FROSTBITE.

Keep oil, grease, and combustibles away. use only equipment cleaned for oxygen service. store and use with adequate ventilation. Do not get liquid in eyes, wear a face shield and gloves. Do not drop. Use suitable hand truck for container movement. Avoid spills. Do not walk on or roll equipment over spills. Cylinder temperature should not exceed 52C (125F). Close valve after each use and when empty. Use in accordance with the Material Safety Data Sheet (MSDS).

FIRST AID: IN CASE OF FROSTBITE, obtain medical treatment immediately.

DO NOT REMOVE LABEL
AIRSERVE, LLC
26770 LIBERAL AVE, CENTER LINE, MI 48015
(586) 427-5349